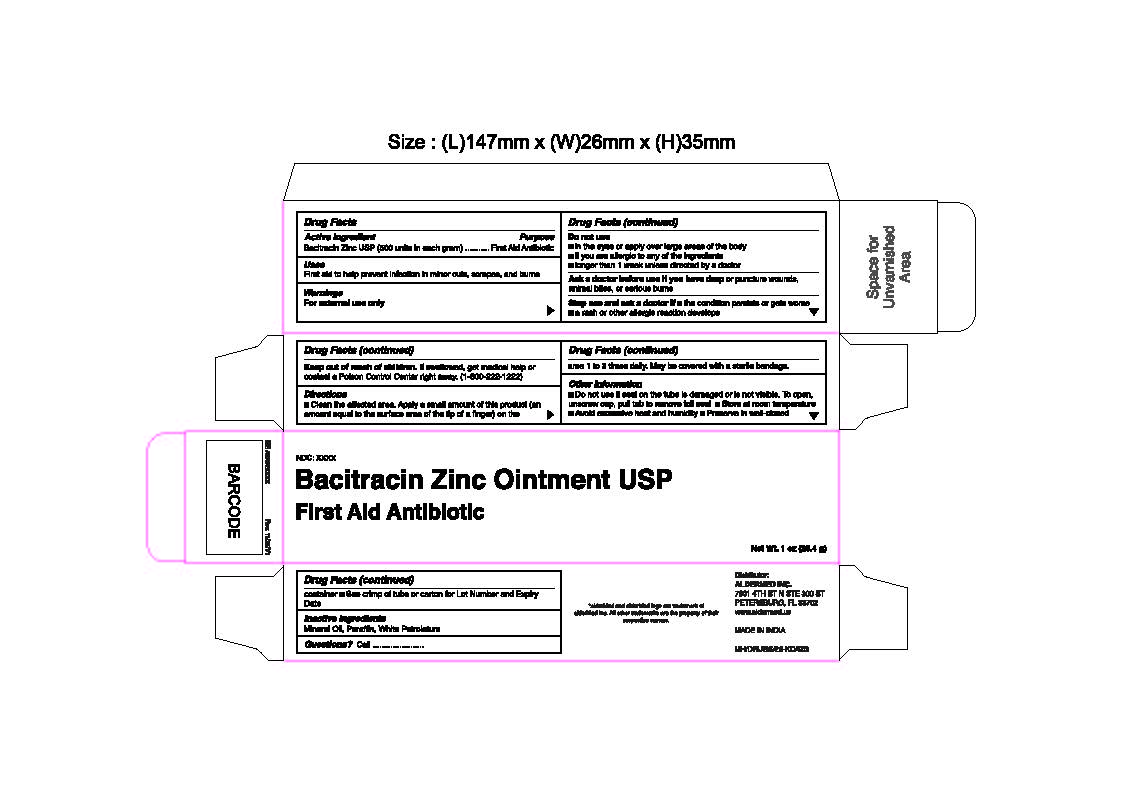 DRUG LABEL: Bacitracin Zinc
NDC: 87236-001 | Form: OINTMENT
Manufacturer: Aldermed Inc.
Category: otc | Type: HUMAN OTC DRUG LABEL
Date: 20260212

ACTIVE INGREDIENTS: BACITRACIN ZINC 500 [USP'U]/1 g
INACTIVE INGREDIENTS: MINERAL OIL; PARAFFIN; WHITE PETROLATUM

Bacitracin Zinc Ointment USP

Active Ingredient

Bacitracin Zinc (500 units in each gram)

Purpose

First Aid Antibiotic

Uses

First aid to help prevent infection in minor cuts, scrapes, and burns

Warnings

For external use only

Do not use

- In the eyes or apply over large areas of the body
- If you are allergic to any of the ingredients
- Longer than 1 week unless directed by a doctor

Ask a doctor before use if you have

deep or puncture wounds, animal bites, or serious burns

Stop use and ask a doctor if

the condition persists or gets worse

if a rash or other allergic reaction develops

Keep out of reach of children

If swallowed, get medical help or contact a Poison Control Center right away.

Directions

Clean the affected area. Apply a small amount of this product (an amount equal to the surface area of the tip of a finger) on the area 1 to 3 times daily. May be covered with a sterile bandage.

Other Information

- Do not use if seal on the tube is damaged or is not visible
- To open,unscrew cap, pull tab to remove foil seal
- Store at room temperature
- Avoid excessive heat and humidity
- Preserve in well-closed container
- See crimp of tube or carton for Lot Number and Expiry Date

Inactive Ingredients

Mineral Oil, Paraffin, White Petrolatum

Questions?

Call 1-833-605-84-74 9am-5 pm EST M-F